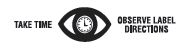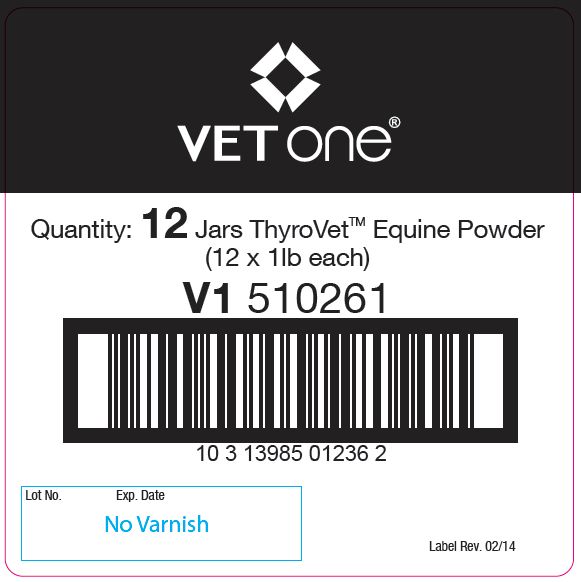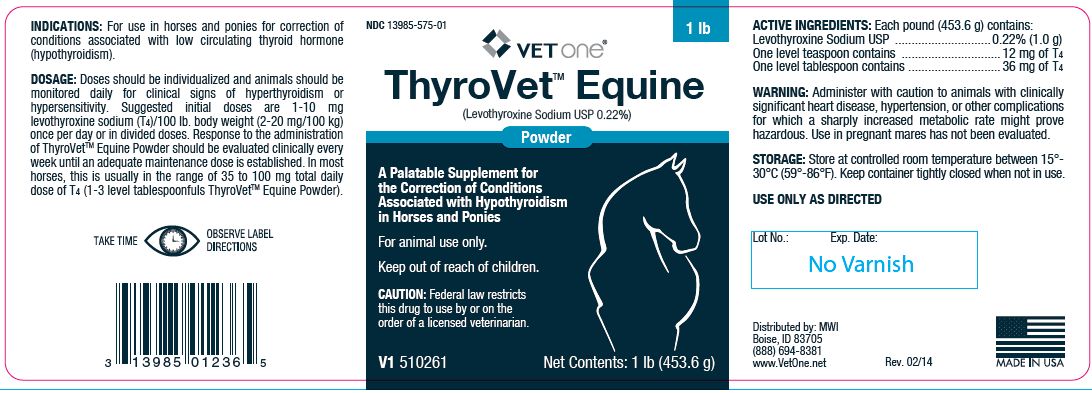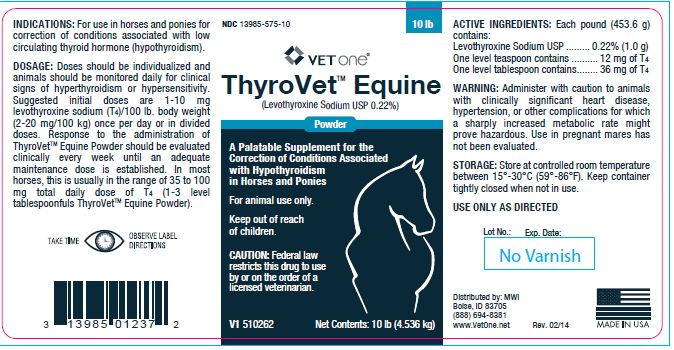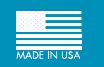 DRUG LABEL: ThyroVet
NDC: 13985-575 | Form: POWDER
Manufacturer: MWI/Vet One
Category: animal | Type: PRESCRIPTION ANIMAL DRUG LABEL
Date: 20231107

ACTIVE INGREDIENTS: LEVOTHYROXINE SODIUM 1000 mg/453.6 g

ThyroVetTM Equine
(Levothyroxine Sodium USP 0.22%)
Powder

VETERINARY INDICATIONS

A Palatable Supplement for the Correction of Conditions Associated with Hypothyroidism in Horses and Ponies

WARNINGS AND PRECAUTIONS

For animal use only.

Keep out of reach of children.

CAUTION: Federal law restricts this drug to use by or on the order of a licensed veterinarian.

INDICATIONS:

For use in horses and ponies for correction of conditions associated with low circulating thyroid hormone (hypothyroidism).

DOSAGE:

Doses should be individualized and animals should be monitored daily for clinical signs of hyperthyroidism or hypersensitivity. Suggested initial doses are 1-10 mg levothyroxine sodium (T4)/100 lb. body weight (2-20 mg/100 kg) once per day or in divided doses. Response to the administration of ThyroVetTM Equine Powder should be evaluated clinically every week until an adequate maintenance dose is established. In most horses, this is usually in the range of 35 to 100 mg total daily dose of T4 (1-3 level tablespoonfuls ThyroVetTM Equine Powder).

ACTIVE INGREDIENTS:

Each pound (453.6 g) contains:
Levothyroxine Sodium USP ............................. 0.22% (1.0 g)
One level teaspoon contains .............................. 12 mg of T4
One level tablespoon contains ............................ 36 mg of T4

WARNING:

Administer with caution to animals with clinically significant heart disease, hypertension, or other complications for which a sharply increased metabolic rate might prove hazardous. Use in pregnant mares has not been evaluated.

STORAGE:

Store at controlled room temperature between 15°- 30°C (59°-86°F). Keep container tightly closed when not in use.

Net Contents:

1 lb (453.6 grams) V1 510261

INFORMATION FOR OWNERS/CAREGIVERS

Distributed by: MWI
Boise, ID 83705
(888) 694-8381
www.VetOne.net